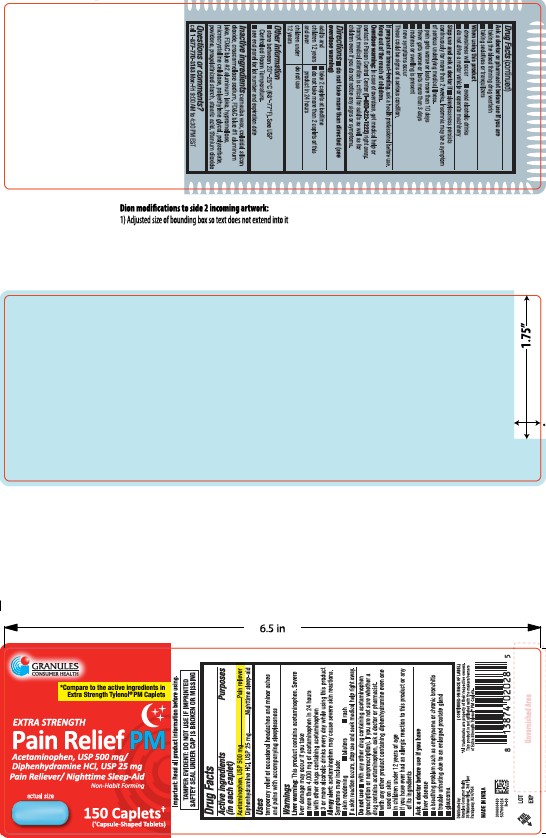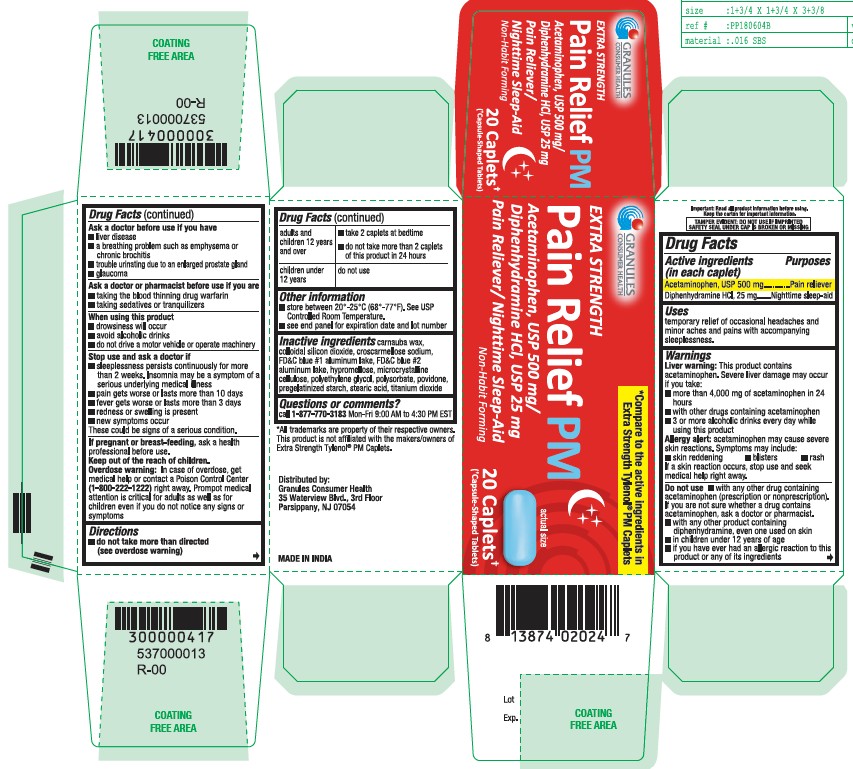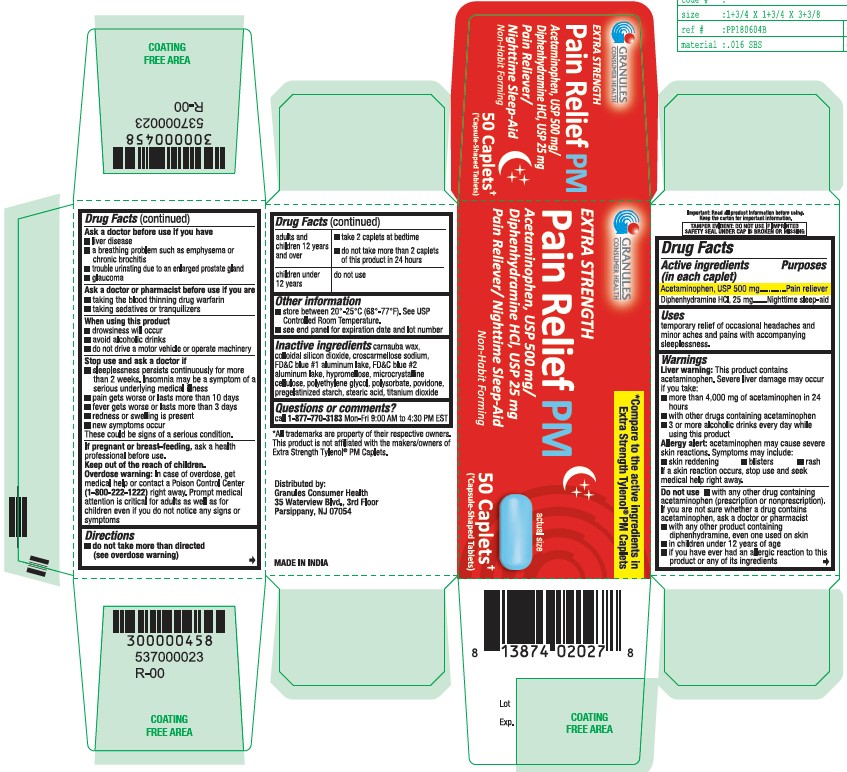 DRUG LABEL: Acetaminophen Diphenhydramine HCl
NDC: 69848-014 | Form: TABLET
Manufacturer: Granules USA, Inc.	
Category: otc | Type: HUMAN OTC DRUG LABEL
Date: 20251222

ACTIVE INGREDIENTS: DIPHENHYDRAMINE HYDROCHLORIDE 25 mg/1 1; ACETAMINOPHEN 500 mg/1 1
INACTIVE INGREDIENTS: FD&C BLUE NO. 2; POLYETHYLENE GLYCOL, UNSPECIFIED; POVIDONE; STEARIC ACID; CROSCARMELLOSE SODIUM; CARNAUBA WAX; SILICON DIOXIDE; FD&C BLUE NO. 1; HYPROMELLOSE, UNSPECIFIED; MICROCRYSTALLINE CELLULOSE; STARCH, CORN; TITANIUM DIOXIDE; POLYSORBATE 80

EXTRA STRENGTH
Pain Relief PM
Acetaminophen, USP 500 mg/ Diphenhydramine HCl, USP 25 mg
Pain Reliever/ Nighttime Sleep-Aid
Non-Habit Forming

Active ingridients

(in each caplet)

Acetaminophen, USP 500mg

Diphenhydramine HCl. 25mg

Purposes

Pain reliever

Nighttime sleep-aid

Uses

temporary relief of occasional headaches and minor aches and pains with accompanying sleeplessness.

Liver warning

This product containsacetaminophen. Severe liver damage may occur if you take:
■ more than 4,000 mg of acetaminophen in 24 hours
■ with other drugs containing acetaminophen
■ 3 or more alcoholic drinks every day while
using this product

Allergy alert

acetaminophen may cause severs skin reactions. Symptoms may include:
■ skin reddening ■ blisters ■ rash
If a skin reaction occurs, stop use and seek medical help right away

DSo not use

■ with any other drug containing acetaminophen (prescription or nonprescription). If you are not sure whether a drug contains
acetaminophen, ask a doctor or pharmacist
■ with any other product containing diphenhydramine, even one used on skin
■ in children under 12 years of age
■ if you have ever had an allergic reaction to this product or any of its ingredients

Ask a doctor before use if you have

■ liver disease
■ a breathing problem such as emphysema or chronic brochitis
■ trouble urinating due to an enlarged prostate gland
■ glaucoma

Ask a doctor or pharmacist before use if you have

■ taking the blood thinning drug warfarin
■ taking sedatives or tranquilizers

When using this product

■ drowsiness will occur
■ avoid alcoholic drinks
■ do not drive a motor vehicle or operate machinery

Stop use and ask a doctor if

■ sleeplessness persists continuously for morethan 2 weeks. Insomnia may be a symptom of a serious underlying medical illness
■ pain gets worse or lasts more t han 10 days
■ fever gets worse or lasts more than 3 days
■ redness or swelling is present
■ new symptoms occur
These could be signs of a serious condition.

If pregnant or breast-feeding

ask a health professional before use.

Overdose warning

In case of overdose, get medical help or contact a Poison Control Center (1-800-222-1222) right away. Prompt medical attention is critical for adults as well as for children even if you do not notice any signs or symptoms.

Directions

■ do not take more than directed (see overdose warning)

adults andchildren 12 years and over

■ take 2 caplets at bedtime do not use
■ do not take more than 2 caplets of this product in 24 hours

children under 12 years

■ do not use

Other information

■ store between 20°-25°C (68°-77°F). See USP Controlled Room Temperature.
■ see end panel for expiration date and lot number

Inactive ingridients

carnauba wax, colloidal silicon dioxide, croscarmellose sodium, FD&C blue #1 aluminum lake, FD&C blue #2 aluminum lake, hypromellose, microcrystalline cellulose, polyethylene glycol, polysorbate, povidone,pregelatinized starch, stearic acid, titanium dioxide